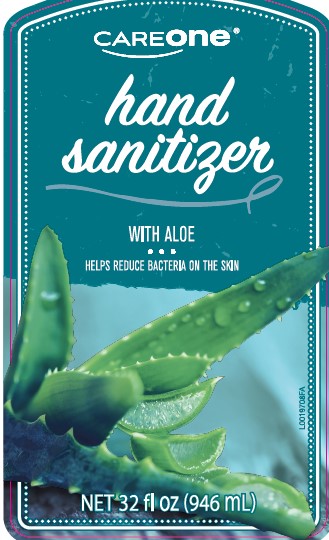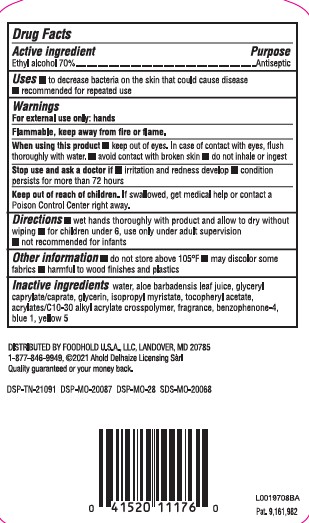 DRUG LABEL: Advanced Hand Sanitizer
NDC: 72476-439 | Form: GEL
Manufacturer: Retail Business Services, LLC 
Category: otc | Type: HUMAN OTC DRUG LABEL
Date: 20260206

ACTIVE INGREDIENTS: ALCOHOL 70 mL/100 mL
INACTIVE INGREDIENTS: WATER; ALOE VERA LEAF; GLYCERYL CAPRYLATE/CAPRATE; GLYCERIN; ISOPROPYL MYRISTATE; .ALPHA.-TOCOPHEROL ACETATE; CARBOMER HOMOPOLYMER, UNSPECIFIED TYPE; CARBOMER INTERPOLYMER TYPE A (ALLYL SUCROSE CROSSLINKED); SULISOBENZONE; FD&C BLUE NO. 1; FD&C YELLOW NO. 5

Care One 439.001/439AB-AC rev1
Advanced Hand Sanitizer with Aloe

Active ingredient

Ethyl alcohol 70%

Purpose

Antiseptic

Uses

- to decrease bacteria on the skin that could cause disease
- recommended for repeated use

Warnings

For external use only: hands

Flammable, keep away from fire or flame.

When using this product

- keep out of eyes. In case of contact with eyes, flush thoroughly with water.
- avoid contact with broken skin
- do not inhale or ingest

Stop use and ask a doctor if

- irritation and redness develop
- condition persists for more than 72 hours

Keep out of reach of children.

If swallowed, get medical help or contact a Poison Control Center right away.

Directions

- wet hands thoroughly with product and allow to dry without wiping
- for children under 6, use only under adult supervision
- not recommended for infants

Other information

- do not store above 105⁰F
- may discolor some fabrics
- harmful to wood finishes and plastics

Inactive ingredients

water, aloe barbadensis leaf juice, glyceryl caprylate/caprate, glycerin, isopropyl myristate, tocopheryl acetate, carbomer or acrylates/C10-30 alkyl acrylate crosspolymer, fragrance, benzophenone-4, blue 1, yellow 5

ADVERSE REACTION

DISTRIBUTED BY FOODHOLD U.S.A., LLC, LANDOVER, MO 20785

1-877-846-9949, 2021 Ahold Delhaize Licensing Sarl

Quality guaranteed or your money back.

DSP-TN-21091 DSP-MO-20087 DSP-MO-28 SDS-MO-20068

Pat. 9,161,982

principal display panel

CAREONE

hand sanitizer

WITH ALOE

HELPS REDUCE BACTERIA ON THE SKIN

NET 32 fl oz (946 mL)